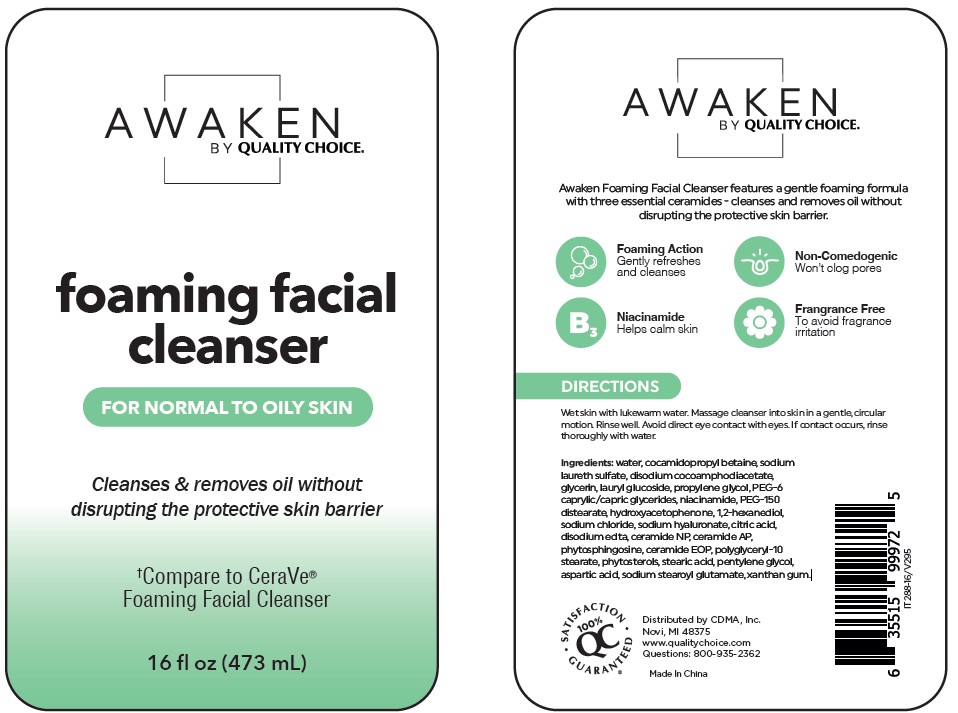 DRUG LABEL: Foaming Facial Cleanser
NDC: 75376-103 | Form: CREAM
Manufacturer: Guangzhou Danting Bath&Body Care Industry Co. Ltd
Category: otc | Type: HUMAN OTC DRUG LABEL
Date: 20250823

ACTIVE INGREDIENTS: GLYCERIN 40 mg/1 mL; NIACINAMIDE 5 mg/1 mL
INACTIVE INGREDIENTS: WATER; COCAMIDOPROPYL BETAINE; SODIUM LAURETH SULFATE; DISODIUM COCOAMPHODIACETATE; LAURYL GLUCOSIDE; PROPYLENE GLYCOL; PEG-6 CAPRYLIC/CAPRIC GLYCERIDES; PEG-150 DISTEARATE; HYDROXYACETOPHENONE; 1,2-HEXANEDIOL; SODIUM CHLORIDE; SODIUM HYALURONATE; CITRIC ACID; EDETATE DISODIUM; CERAMIDE NP; CERAMIDE AP; PHYTOSPHINGOSINE; CERAMIDE 1; POLYGLYCERYL-10 STEARATE; STEARIC ACID; PENTYLENE GLYCOL; ASPARTIC ACID; SODIUM STEAROYL GLUTAMATE; XANTHAN GUM

QC Foaming Facial Cleanser

Active Ingredient

Glycerin 4%

Niacinamide 0.5%

PURPOSE

Skin Protectant

DOSAGE AND ADMINISTRATION

Skin Protectant

WARNINGS

If contact with eyes occurs, rinse thoroughly with water.

WHEN USING

Avoid eye area

INDICATIONS AND USAGE

Wet skin with lukewarm water. Massage cleanser into skin in a gentle, circular
motion. Rinse well.

STORAGE AND HANDLING

Store in a cool, dark place